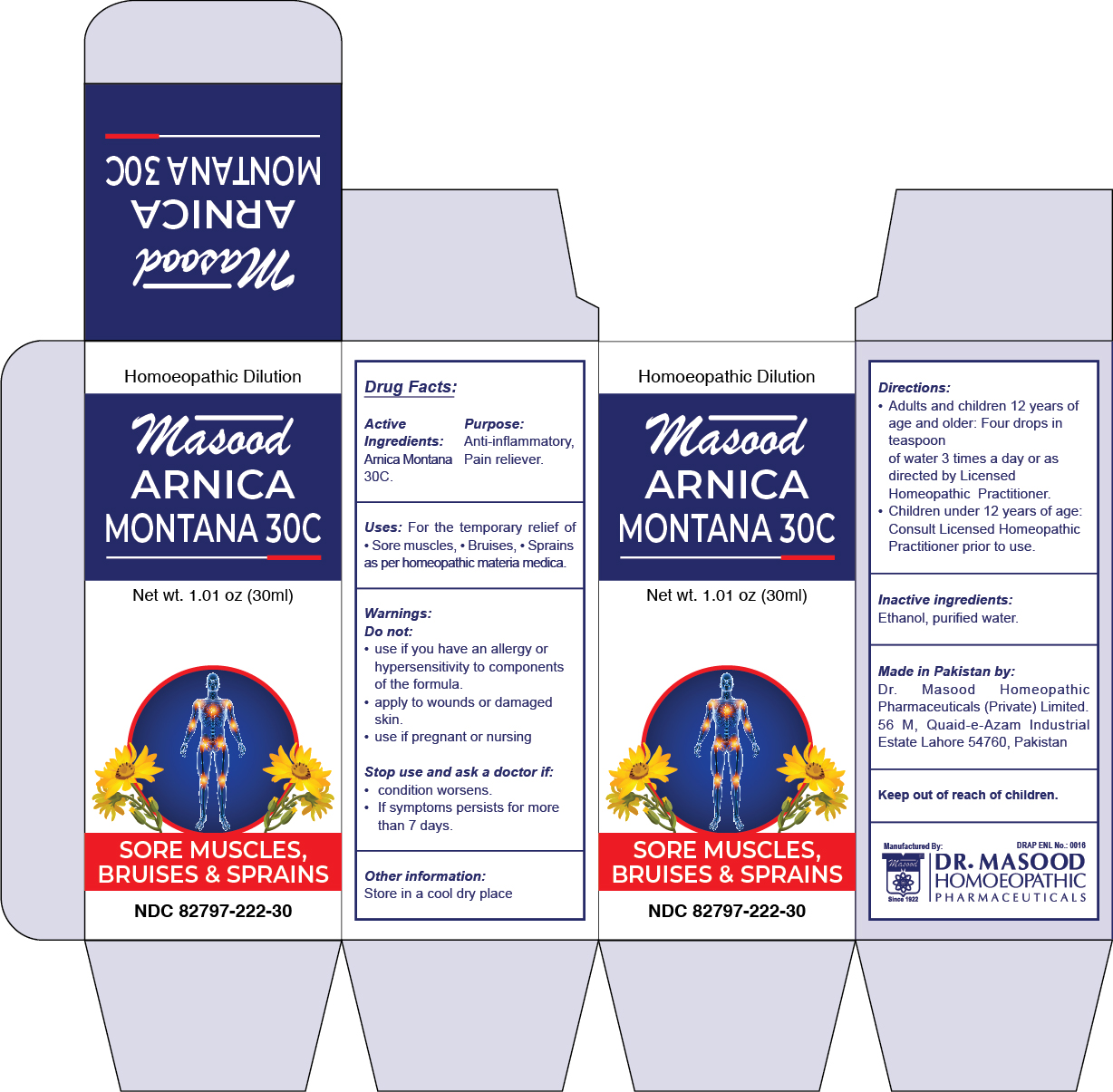 DRUG LABEL: Masood Arnica Montana 30 C
NDC: 82797-222 | Form: LIQUID
Manufacturer: Dr. Masood Homeopathic Pharmaceuticals Private Limited
Category: homeopathic | Type: HUMAN OTC DRUG LABEL
Date: 20240109

ACTIVE INGREDIENTS: ARNICA MONTANA FLOWER 30 [hp_C]/30 mL
INACTIVE INGREDIENTS: 2-(ETHYLTHIO)ETHANOL 27 mL/30 mL; WATER 2.7 mL/30 mL

Arnica Montana Dilution

Directions:

- Adults and children 12 years of age and older: Four drops in teaspoon of water 3 times a day or as directed by Licensed Homeopathic Practitioner.
- Children under 12 years of age: Consult Licensed Homeopathic Practitioner prior to use.

Uses:

- For the temporary relief of
- Sores muscles, bruises, sprains as per homeopathic materia medica

Inactive ingredients:

Ethanol, purified water

Active Ingredients

Arnica Montana 30 C

Keep out of reach of children.

Purpose

Anti-inflammatory, Pain reliever

Warnings:

Do not:

- use if you have an allergy or hypersensitivity to components of the formula
- apply to wounds or damaged skin
- use if pregnant or nursing,

Stop use and ask a doctor if:

- condition worsens
- If symptoms persists for more than 7 days